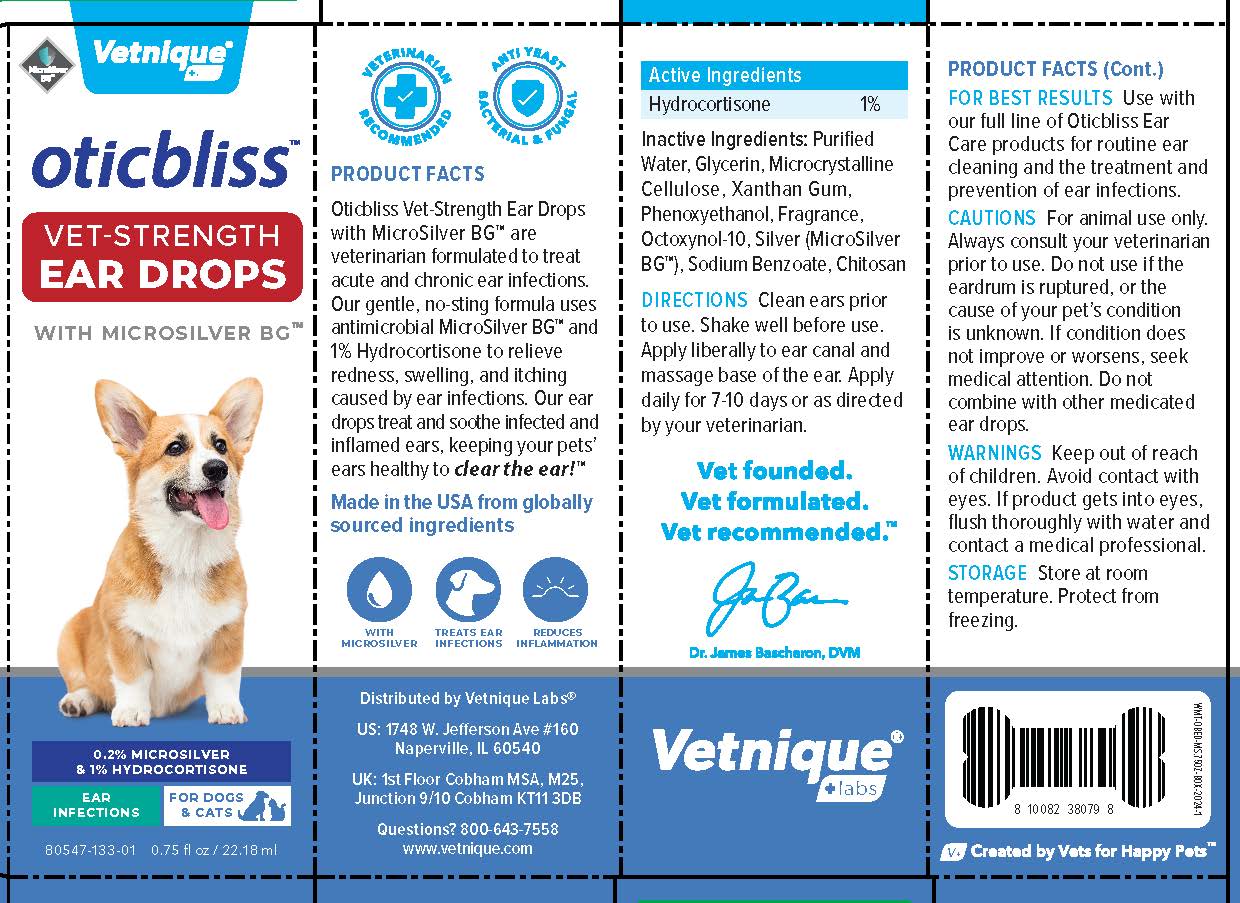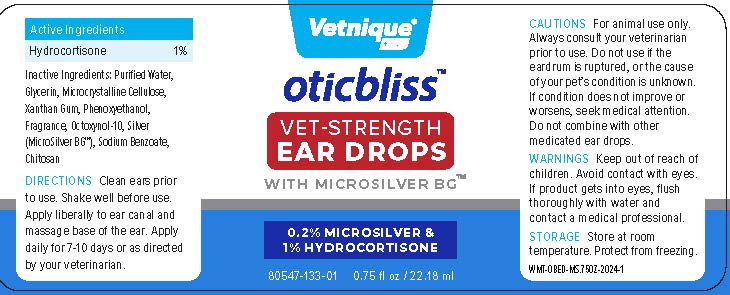 DRUG LABEL: Oticbliss Vet Strength Microsilver Ear Drops
NDC: 80547-133 | Form: SOLUTION/ DROPS
Manufacturer: Vetnique Labs LLC
Category: animal | Type: OTC ANIMAL DRUG LABEL
Date: 20241111

ACTIVE INGREDIENTS: Hydrocortisone 1 g/100 g
INACTIVE INGREDIENTS: WATER; Glycerin; Microcrystalline Cellulose; Xanthan Gum; PHENOXYETHANOL; Octoxynol-10; SILVER; CHITOSAN HIGH MOLECULAR WEIGHT (400-800 MPA.S)

Vetnique Labs LLC - Oticbliss Vet Strength Microsilver Ear Drops

Active Ingredients

Hydrocortisone 1%

Inactive Ingredients:

Purified Water, Glycerin, Microcrystalline Cellulose, Xanthan Gum, Phenoxyethanol, Fragrance, Octoxynol-10, Silver (MicroSilver BG™), Sodium Benzoate, Chitosan